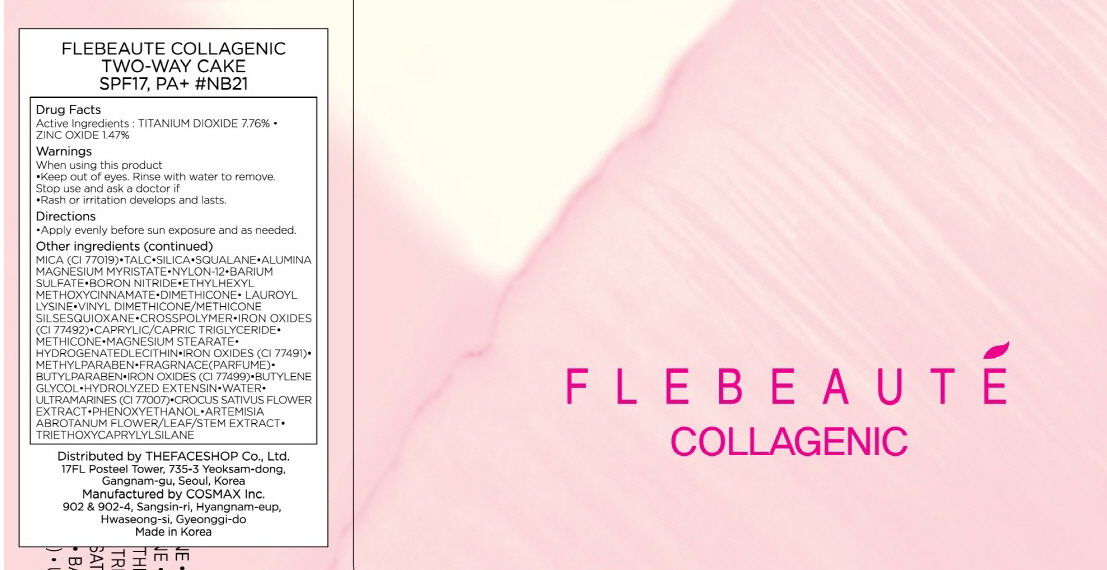 DRUG LABEL: FLEBEAUTE COLLAGENIC TWO WAY CAKE
NDC: 51523-009 | Form: POWDER
Manufacturer: THEFACESHOP CO., LTD.
Category: otc | Type: HUMAN OTC DRUG LABEL
Date: 20100713

ACTIVE INGREDIENTS: TITANIUM DIOXIDE 0.93 g/12 g; ZINC OXIDE 0.17 g/12 g

Drug Facts

Active Ingredients: TITANIUM DIOXIDE, ZINC OXIDE

Inactive Ingredients:
MICA(CI 77019), TALC, SILICA, SQUALANE, ALUMINA MAGNESIUM MYRISTATE, NYLON-12, BARIUM SULFATE, BORON NITRIDE, ETHYLHEXYL METHOXYCINNAMATE, DIMETHICONE, LAUROYL LYSINE, VINYL DIMETHICONE/METHICONE SILSESQUIOXANE, CROSSPOLYMER, IRON OXIDES(CI 77492), CAPRYLIC/CAPRIC TRIGLYCERIDE, METHICONE, MAGNESIUM STEARATE, HYDROGENATED LECITHIN, IRON OXIDES(CI 77491), METHYLPARABEN, FRAGRNACE, BUTYLPARABEN, IRON OXIDES(CI 77499), BUTYLENE GLYCOL, HYDROLYZED EXTENSIN, WATER, ULTRAMARINES(CI 77007), CROCUS SATIVUS FLOWER EXTRACT, PHENOXYETHANOL, ARTEMISIA ABROTANUM FLOWER/LEAF/STEM EXTRACT, TRIETHOXYCAPRYLYLSILANE

Warnings:
When using this product
Keep out of eyes. Rinse with water to remove.
Stop use and ask a doctor if
Rash or irritation develops and lasts.
Directions:
Apply evenly before sun exposure and as needed.